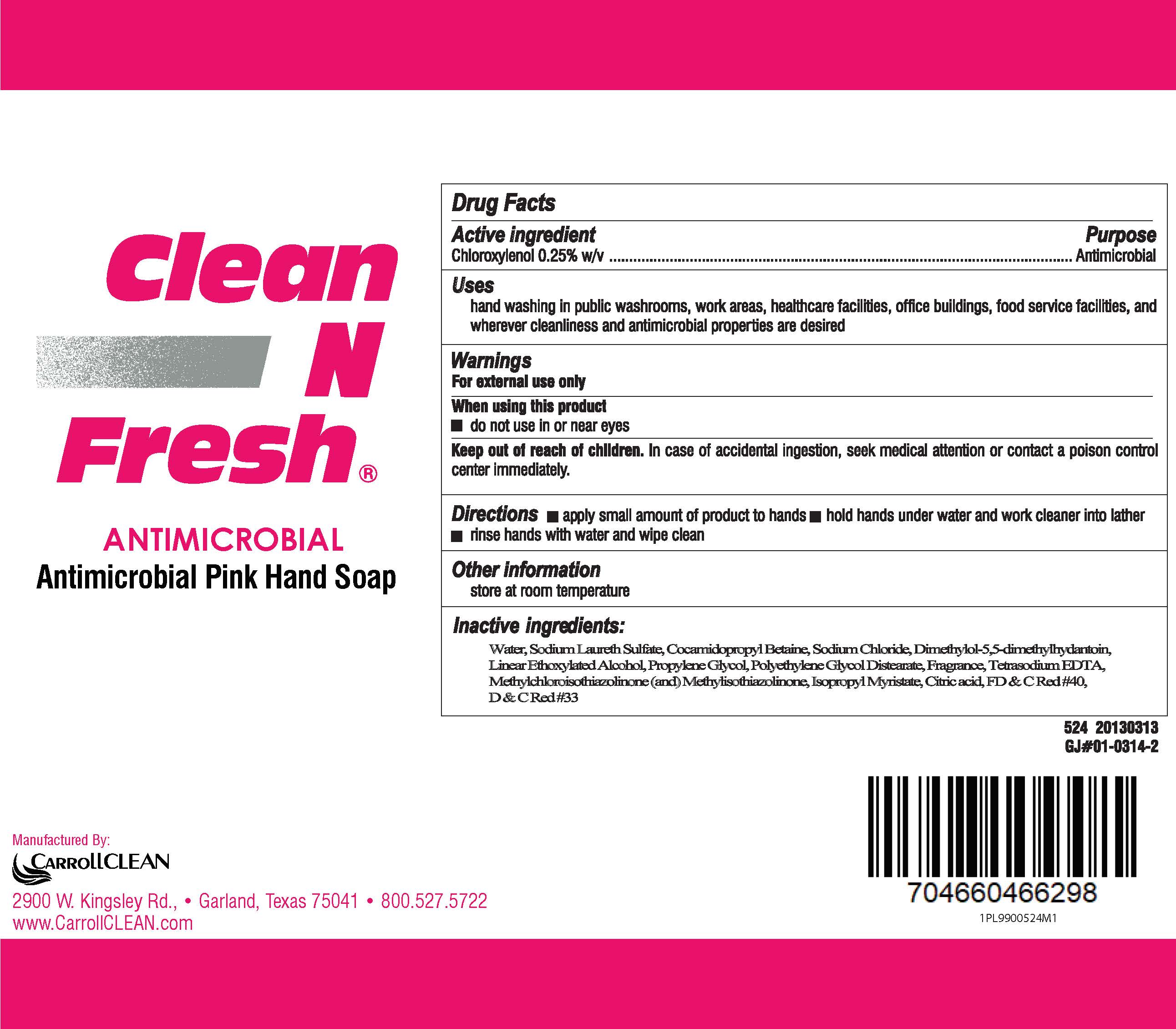 DRUG LABEL: CarrollCLEAN
NDC: 73708-524 | Form: SOAP
Manufacturer: CarrollCLEAN LCC
Category: otc | Type: HUMAN OTC DRUG LABEL
Date: 20201106

ACTIVE INGREDIENTS: CHLOROXYLENOL 0.282 mg/100 mL
INACTIVE INGREDIENTS: SODIUM LAURETH-3 SULFATE 7.85 mL/100 mL; METHYLCHLOROISOTHIAZOLINONE/METHYLISOTHIAZOLINONE MIXTURE 0.099 mL/100 mL; COCAMIDOPROPYL BETAINE 4.132 mL/100 mL; C9-11 PARETH-8 0.242 mL/100 mL; ANHYDROUS CITRIC ACID 0.005 mL/100 mL; PEG-150 DISTEARATE 0.317 mL/100 mL; WATER 84.307 mL/100 mL; ISOPROPYL MYRISTATE 0.026 mL/100 mL; SODIUM CHLORIDE 2.146 mL/100 mL; D&C RED NO. 33 0.0004 mL/100 mL; EDETATE SODIUM TETRAHYDRATE 0.038 mL/100 mL; PROPYLENE GLYCOL 0.221 mL/100 mL; FD&C RED NO. 40 0.0002 mL/100 mL; DMDM HYDANTOIN 0.334 mL/100 mL

Pink antimicrobial soap

Active ingredient

Chloroxylenol 0.25% w/v

Purpose

Antimicrobial

Uses

- hand washing in public washrooms, work areas, healthcare facilities, office buildings, food service facilities, and whatever cleanliness and antimicrobial properties are desired.

Warnings

For external use only

When using this product

- do not use in or near eyes

Keep out of reach of children

In case of accidental ingestion, seek medical attention or contact a poison control center immediately.

Directions

- apply small amount of product to hands
- hold hands under water and work cleaner into lather
- rinse with water and wipe clean

Other information

- store at room temperature

Inactive ingredients section

Water, Sodium Laureth Sulfate, Cocamidopropyl Betaine, Sodium Chloride, Dimethylol-5,5-dimethylhydantoin, Linear Ethoxylated Alcohol, Propylene Glycol, Polyethylene Glycol Distereate, Fragance, Tetrasodium EDTA, Methylchloroisothiazolinone (and) Methyllisothiazolinone, Isopropyl Myristate, Citric acid, FD & C Red #40, D & C Red #33